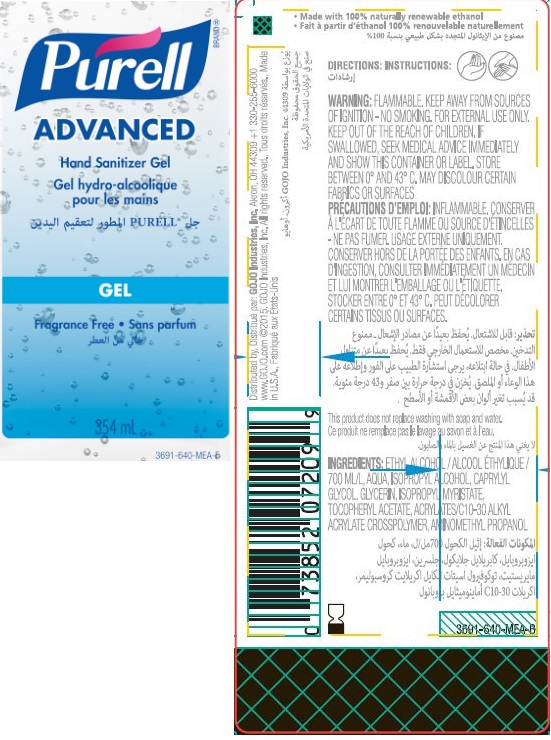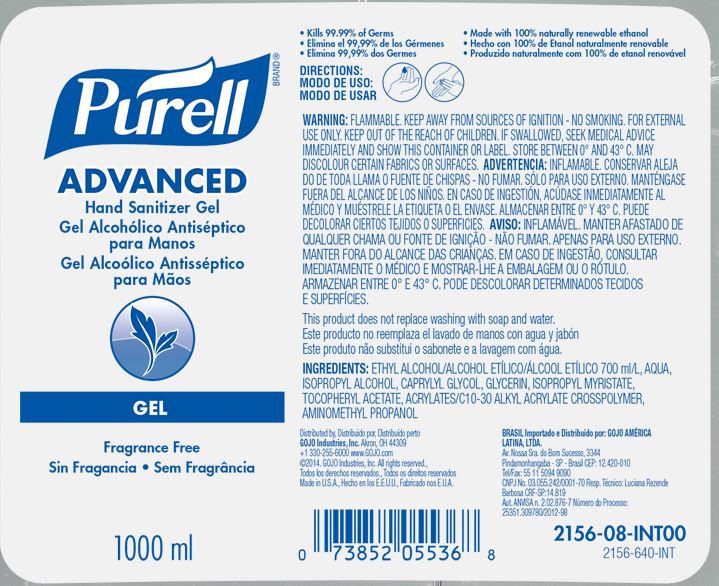 DRUG LABEL: PURELL Advanced Hand Sanitizer Gel
NDC: 21749-032 | Form: GEL
Manufacturer: GOJO Industries, Inc.
Category: otc | Type: HUMAN OTC DRUG LABEL
Date: 20260112

ACTIVE INGREDIENTS: ALCOHOL 0.7 mL/1 mL
INACTIVE INGREDIENTS: WATER; ISOPROPYL ALCOHOL; CAPRYLYL GLYCOL; GLYCERIN; ISOPROPYL MYRISTATE; .ALPHA.-TOCOPHEROL ACETATE; CARBOMER INTERPOLYMER TYPE A (ALLYL SUCROSE CROSSLINKED); AMINOMETHYLPROPANOL

PURELL Advanced Hand Sanitizer Gel